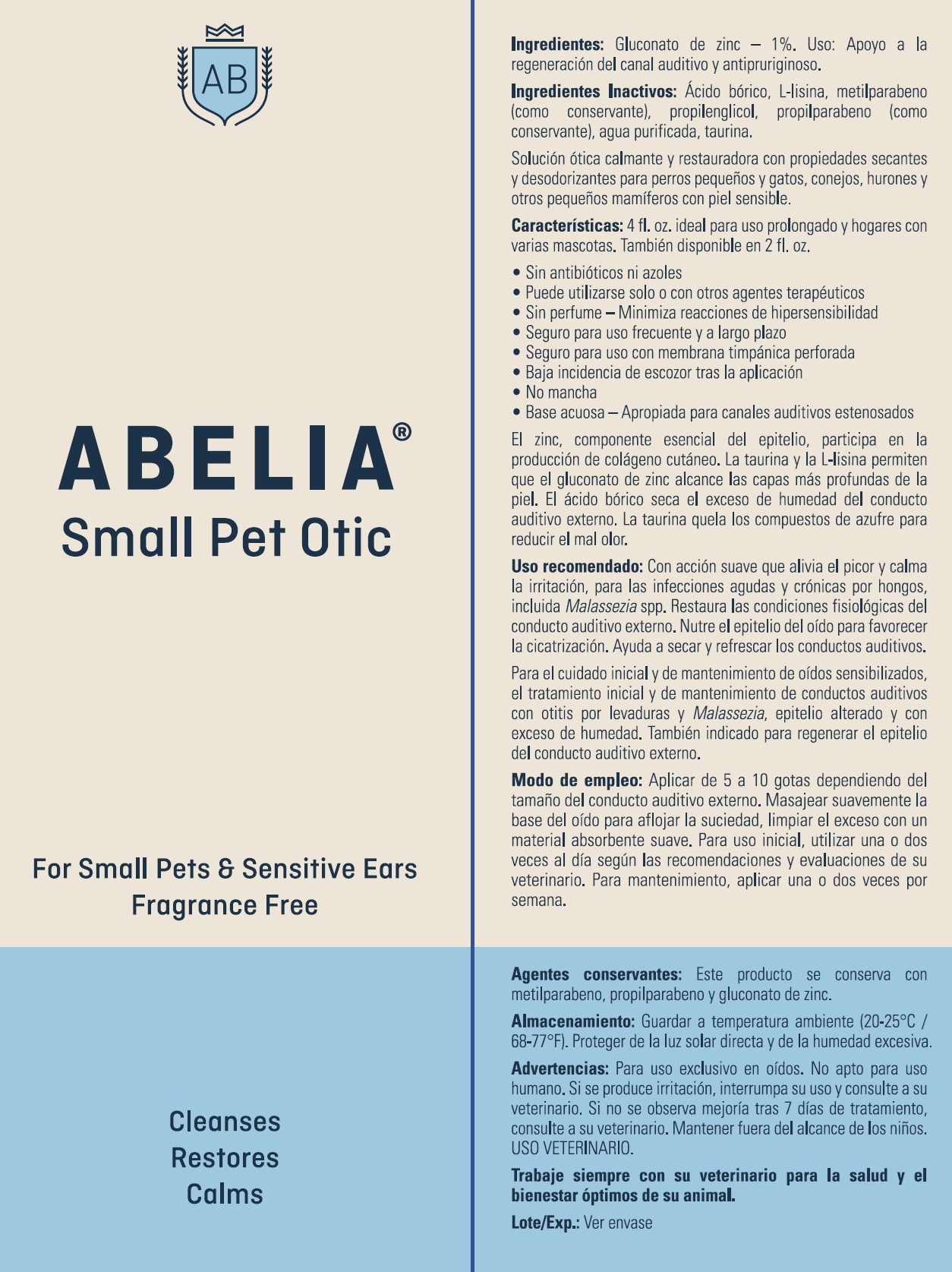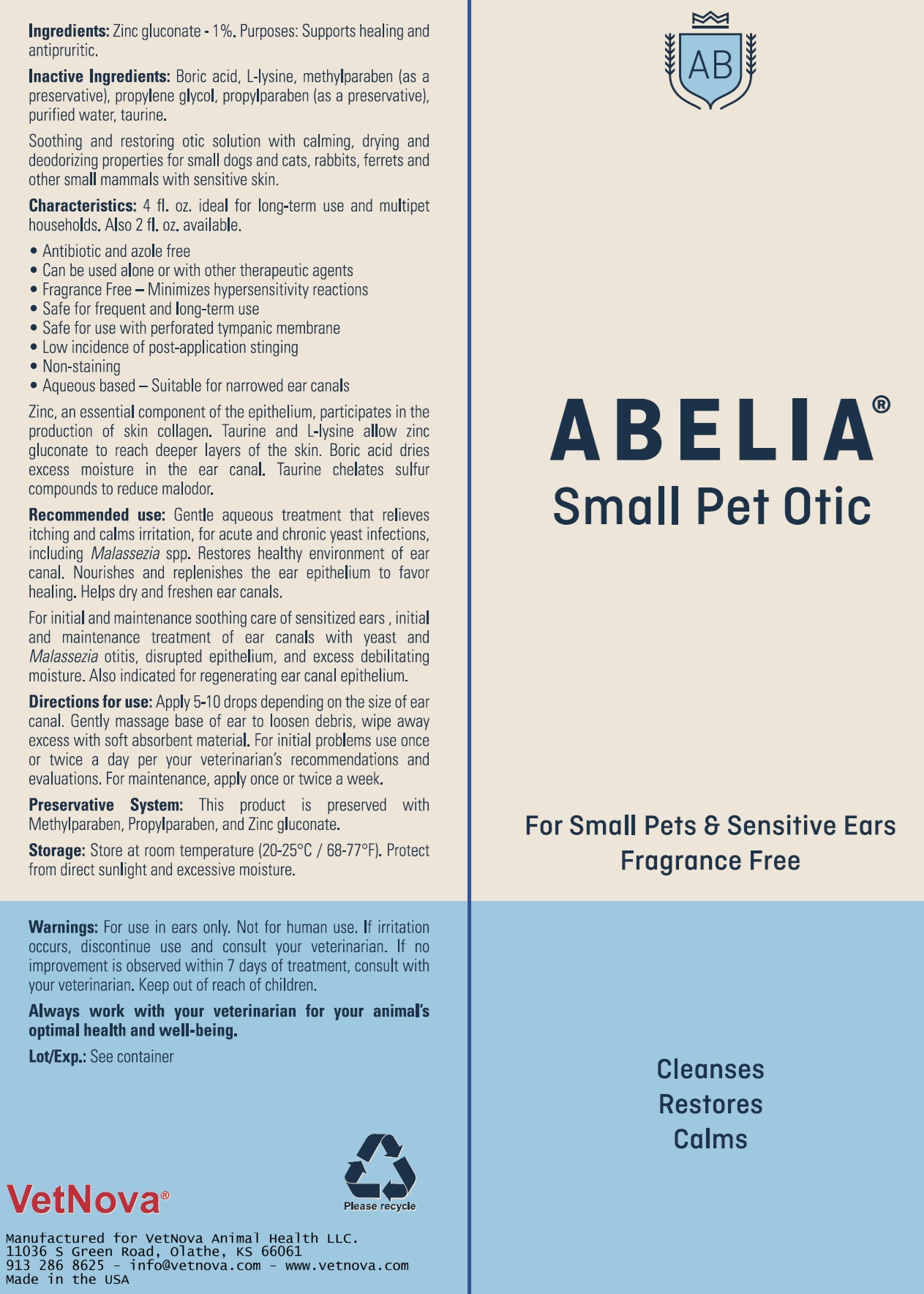 DRUG LABEL: Abelia Small Pet Otic
NDC: 86145-200 | Form: SOLUTION/ DROPS
Manufacturer: Vetnova Animal Health LLC
Category: animal | Type: OTC ANIMAL DRUG LABEL
Date: 20251117

ACTIVE INGREDIENTS: zinc gluconate 10 mg/1 mL
INACTIVE INGREDIENTS: Boric Acid; LYSINE; taurine; WATER; Methylparaben; Propylparaben

Abelia™ Small Pet Otic

VETERINARY INDICATIONS

Antimicrobial, drying, deodorizing, soothing and protective otic solution for rabbits, ferrets and other small mammals. Ideal for very sensitive ears especially in pocket pets, exotic mammals, kittens, puppies and small breeds of dogs and cats. Can be used alone or with other therapeutic agents.

Gentle aqueous treatment for acute and chronic yeast infections including Malassezia spp. Relieves itching and calms irritation. Restores healthy environment of ear canal. Nourishes and replenishes epithelium to favor healing. Helps dry and freshen ear canal. Does not interfere with allergy tests. Stain and oil free on fur, pets beds and furniture. Antibiotic and corticosteroid free.

INDICATIONS AND USAGE

Indications: for initial and maintenance treatment of ear canals with yeast adnd Malassezia spp. otitis, disrupted epithelium, and excess debilitating moisture. For regenerating ear canal epithelium after treatment of ear mites in rabbits, ferrets and kittens. Safe for frequent and long-term use. Safe for use with perforated tympanic membrane.

DOSAGE AND ADMINISTRATION

Directions: apply 5-10 drops depending on size of ear canal. Gently massage base of ear to loosen debris, wipe away excess with soft absorbent material. For initial problems use once or twice a day per your veterinarian's recommendations and evaluations. For maintenance, apply once or twice a week.

DESCRIPTION

Ingredients: deionized water, zinc gluconate, boric acid, l-lysine, propylene glycol, taurine, methylparaben, propylparaben.

PRECAUTIONS

Cautions: for animal and topical use only. Avoid contact with eyes. If irritation develops or increases discontinue use and consult your veterinarian. Keep out of reach of children and animals. Store at room temperature.

Always work with your veterinarian for your animals optimal health and well-being.

Para información en español, visite nuestra página www.vetnova.com

Please recycle

Manufactured for VetNova Animal Health LLC
11036 S Green Rd. Olathe, KS 66061
info@vetnova.com • 913 279 1224 • www.vetnova.com
Made in the USA

PRINCIPAL DISPLAY PANEL - 59 ml Bottle Box

ABELIA™
Small Pet Otic

Otic Solution for Small Pets

Cleanses
Restores
Calms